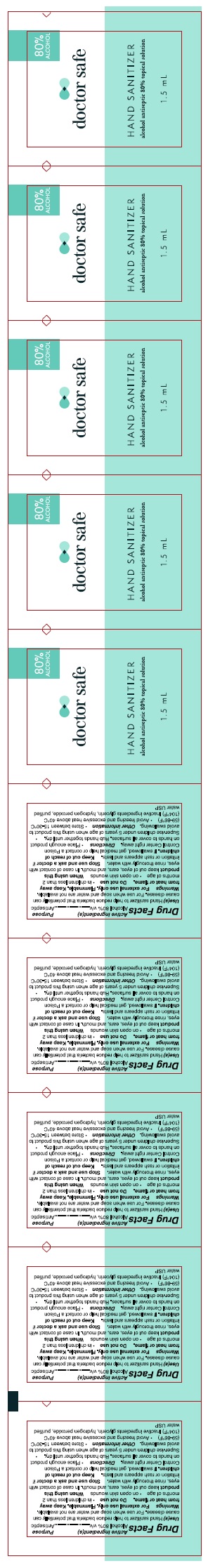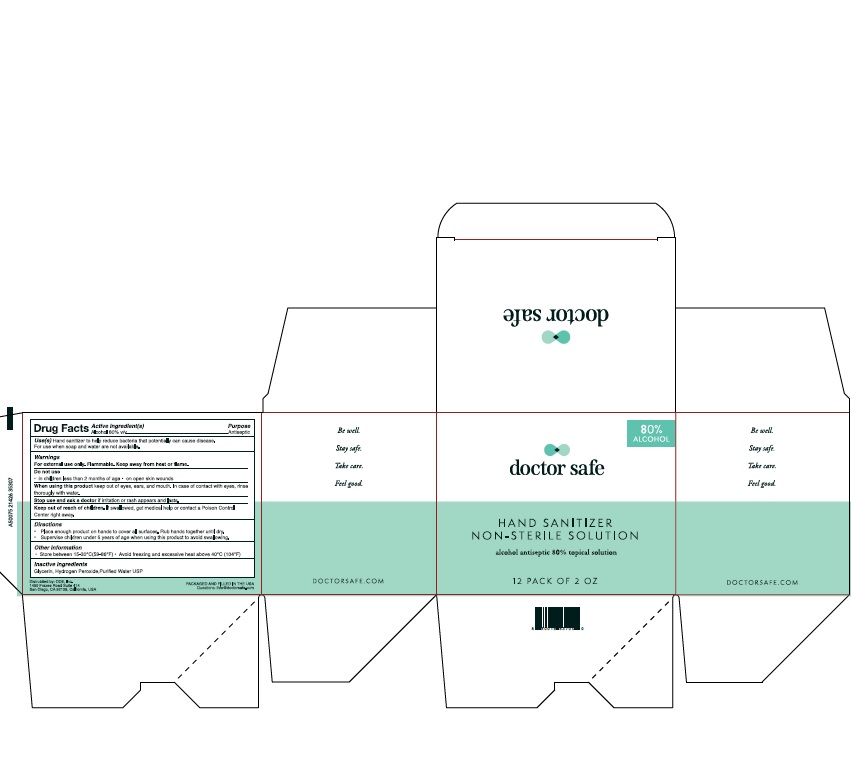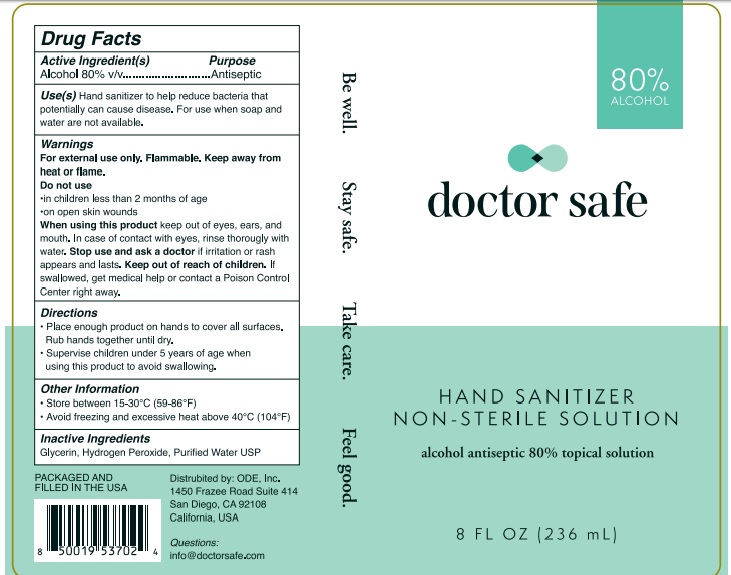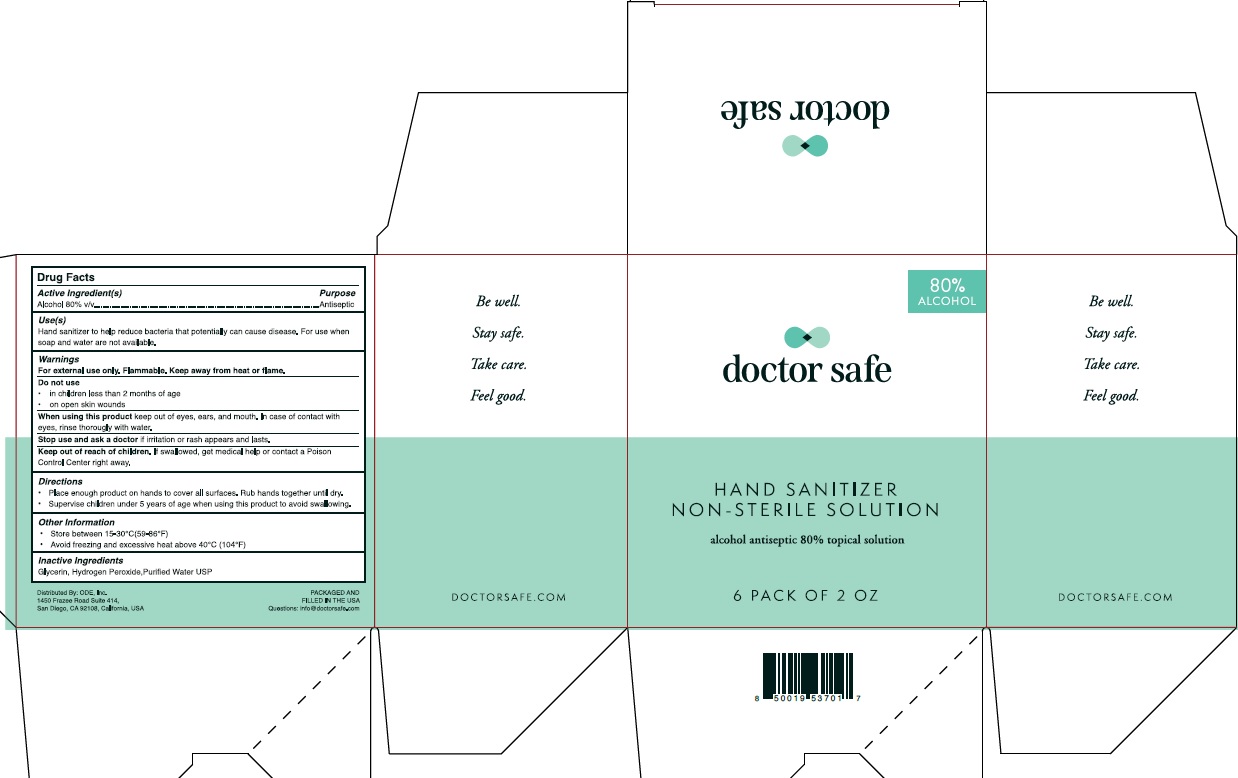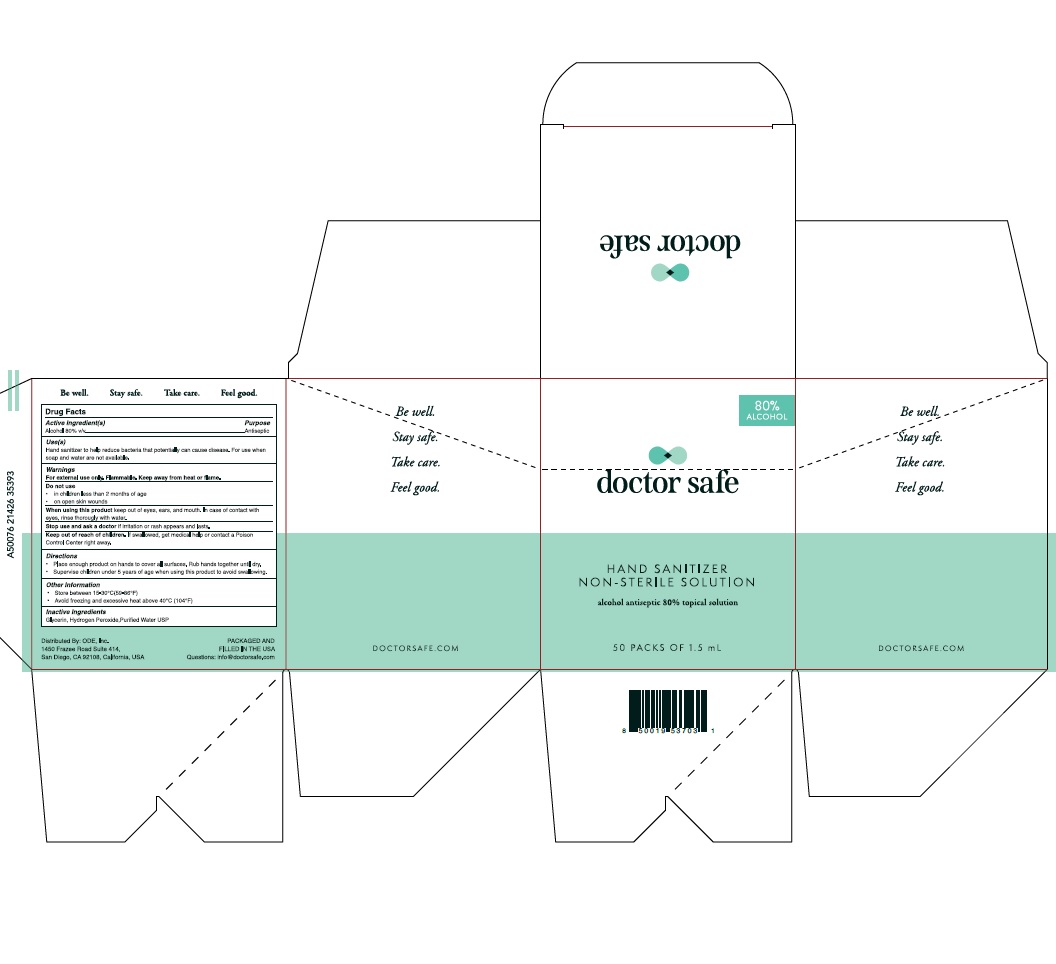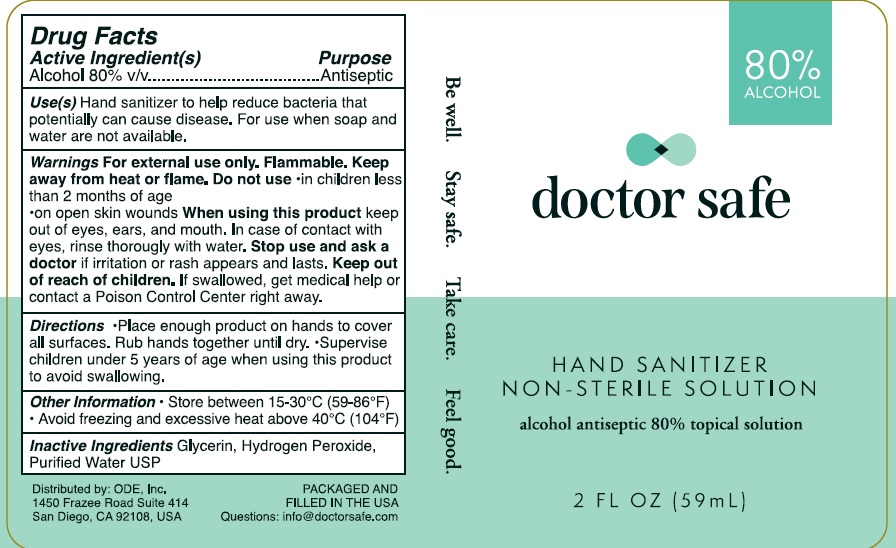 DRUG LABEL: DOCTOR SAFE
NDC: 78542-001 | Form: GEL
Manufacturer: ONE DIAMOND ELECTRONICS, INC.
Category: otc | Type: HUMAN OTC DRUG LABEL
Date: 20200529

ACTIVE INGREDIENTS: ALCOHOL 80 mL/100 mL
INACTIVE INGREDIENTS: HYDROGEN PEROXIDE; WATER; GLYCERIN

DOCTOR SAFE

Active Ingredient

Alcohol 80% v/v

Purpose

Antiseptic

Warnings

For external use only. Flammable. Keep away from heat or flame.

Do not use:

1) in children less than 2 months of age;

2) on open skin wounds.

When using this product keep out of eyes, ears, and mouth.

In case of contact with eyes, rinse eyes thoroughly with water.

Stop use and ask a doctor if irritation or rash occurs.

These may be signs of a serious condition.

If swallowed, get medical help, or contact a Poison Control Center right away.

Uses

Hand Sanitizer to help reduce bacteria that potentially can cause disease.

For use when soap and water are not available.

Directions

1) Place enough product on hands to cover all surfaces. Rub hands together until dry;

2) Supervise children under 6 years of age when using this product to avoid swallowing.

Keep out of reach of children.

If swallowed, get medical help, or contact a Poison Control Center right away

Other Information

1) Store between 15-30C (59-86F);

2)Avoid freezing and excessive heat above 40C (104F

Inactive Ingredient

Glycerin, Hydrogen peroxide, Purified water USP.